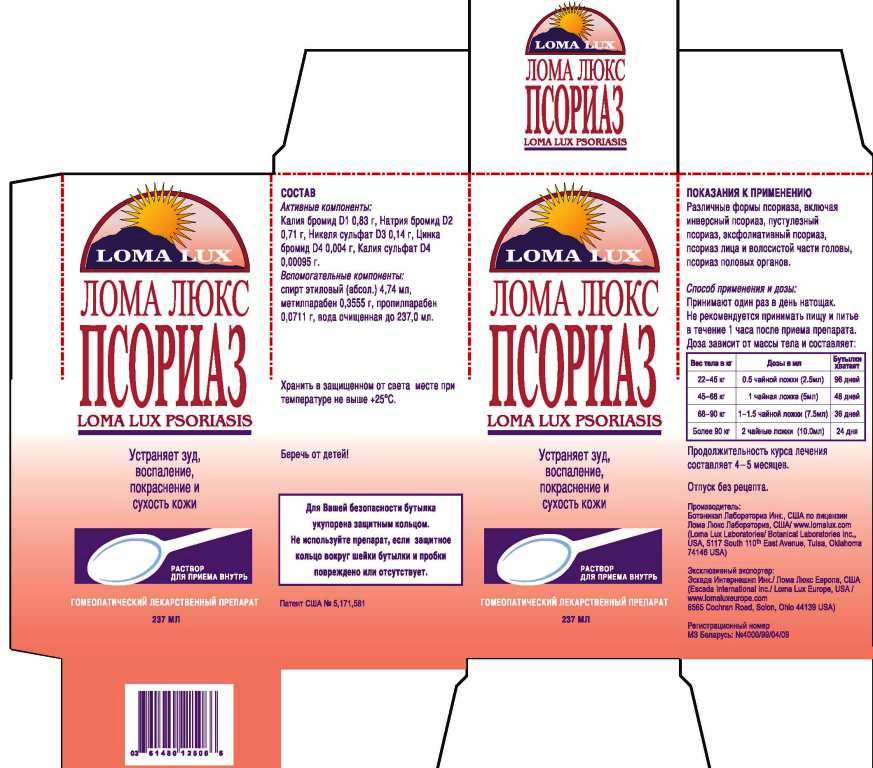 DRUG LABEL: Loma Lux Psoriasis 
NDC: 57520-0713 | Form: LIQUID
Manufacturer: Apotheca Company
Category: homeopathic | Type: HUMAN OTC DRUG LABEL
Date: 20110707

ACTIVE INGREDIENTS: POTASSIUM BROMIDE 1 [hp_X]/1 mL; SODIUM BROMIDE 2 [hp_X]/1 mL; NICKEL SULFATE HEXAHYDRATE 3 [hp_X]/1 mL; POTASSIUM SULFATE 4 [hp_X]/1 mL; ZINC BROMIDE 4 [hp_X]/1 mL
INACTIVE INGREDIENTS: WATER; ALCOHOL; METHYLPARABEN; PROPYLPARABEN

Loma Lux Psoriasis

ACTIVE INGREDIENT

ACTIVE INGREDIENTS: Kali Bromatum 1X, Natrum bromatum 2X, Niccolum sulphuricum 3X, Kali sulphuricum 4X, Zincum bromatum 4X.

PURPOSE

For relief from the scaling, itching and redness of Psoriasis and Seborrhea.

WARNINGS: Do not use if pregnant or nursing.

If allergic to nickel or costume jewelry, use only under the advice and supervision of a physician.

If symptoms worsen, contact a physician.

Keep out or the reach of children.

CAUTION: Use only as directed.

Do not give to children under ten years old or use in the presence of kidney disease.

If skin rash appears or if nervous symptoms persist, recur frequently or are unusual, discontinue use and consult a physician.

DOSAGE AND ADMINISTRATION

DIRECTIONS: Take medication orally at the beginning of the day before eating or drinking anything other than water. Take nothing but water for one hour after taking medication in order to improve absorption. Continue LOMA LUX PSORIASIS as long as it is beneficial to your overall condition. Recommended minimum duration of treatment is 4-5 months.

Weight Daily Dosage Bottle Lasts

50-100 lbs 1/2 tsp 96 days

100-150 lbs 1 tsp 48 days

150-200 lbs 1 1/2 tsp 36 days

Over 200 lbs 2 tsp 24 days

INACTIVE INGREDIENT

INACTIVE INGREDIENTS: Purified water, USP alcohol 2%, methylparaben 0.15%, propylparaben 0.03%.

KEEP OUT OF THE REACH OF CHILDREN.

INDICATIONS AND USAGE

For relief from the scaling, itching and redness of Psoriasis and Seborrhea.

QUESTIONS

Manufactured for and dist. by:

LOMA LUX LABORATORIES

P.O. BOX 702418

TULSA, OK 74170-2418

Questions? Call us!

800-316-9636

More information? Visit our web site:

www.lomalux.com

PACKAGE LABEL

LOMA LUX

LOMA LUX PSORIASIS

For relief from the scaling, itching and redness of Psoriasis and Seborrhea

TAKE ORALLY

HOMEOPATHIC MEDICINE

8 FL. OZ. (237 ml)